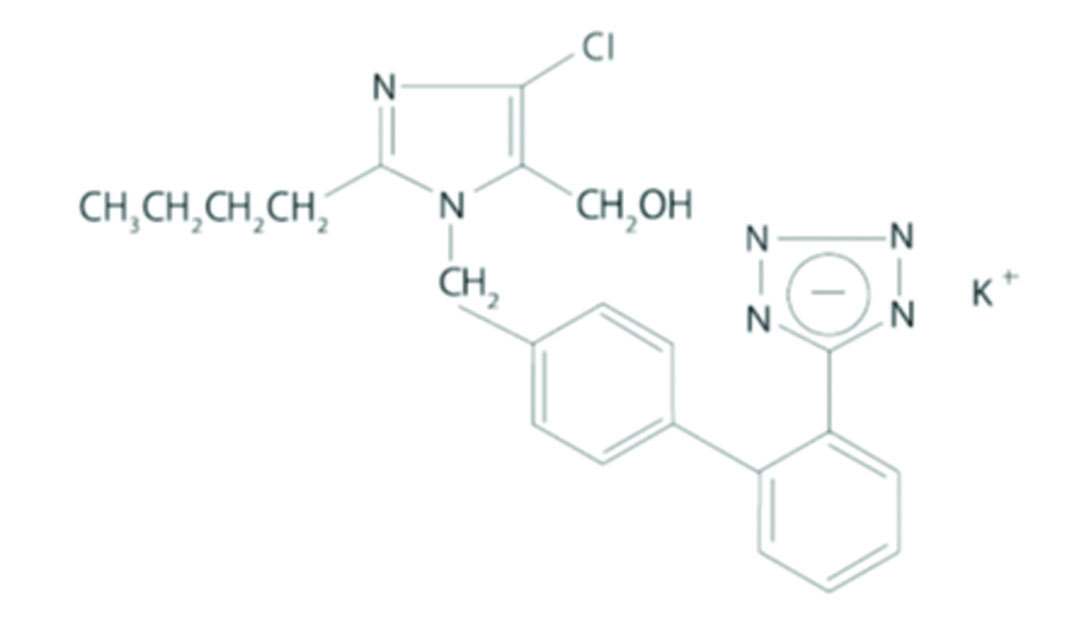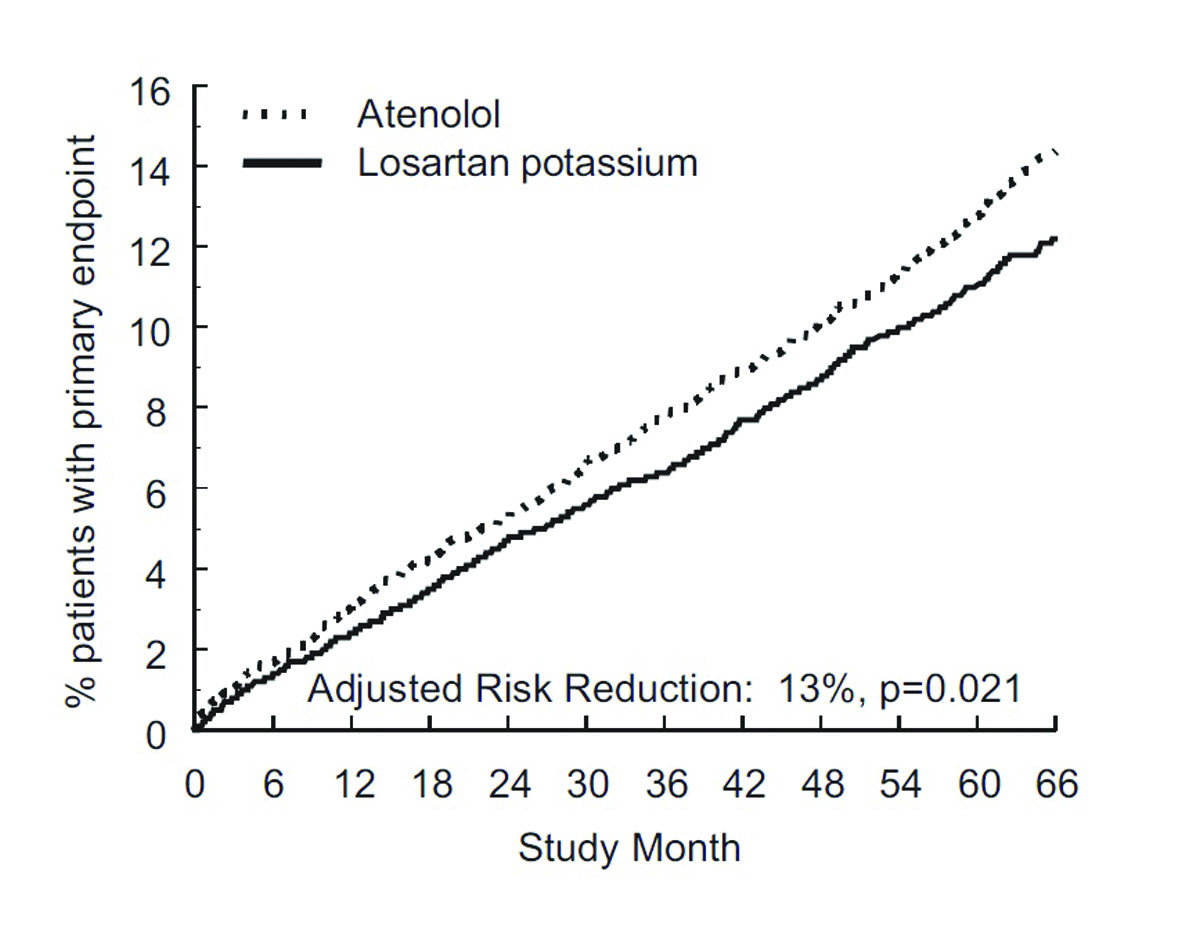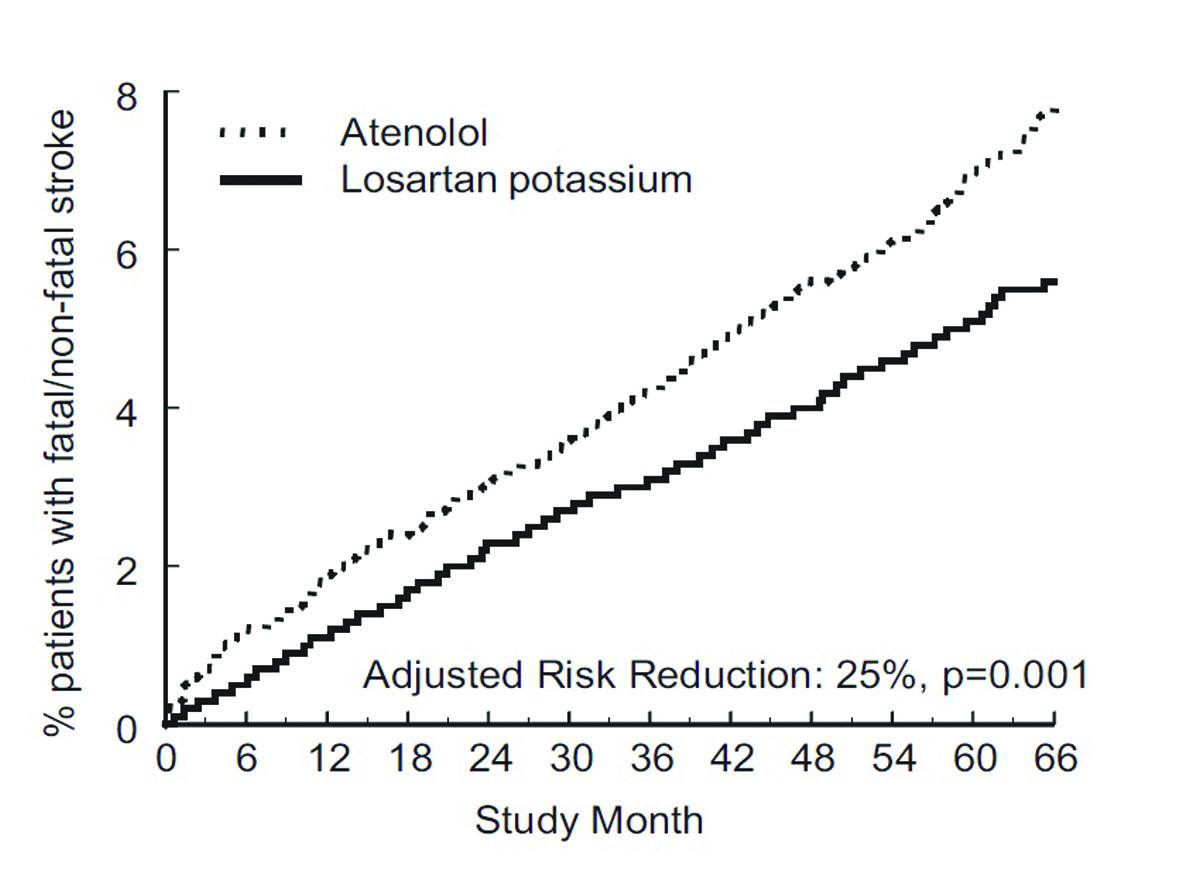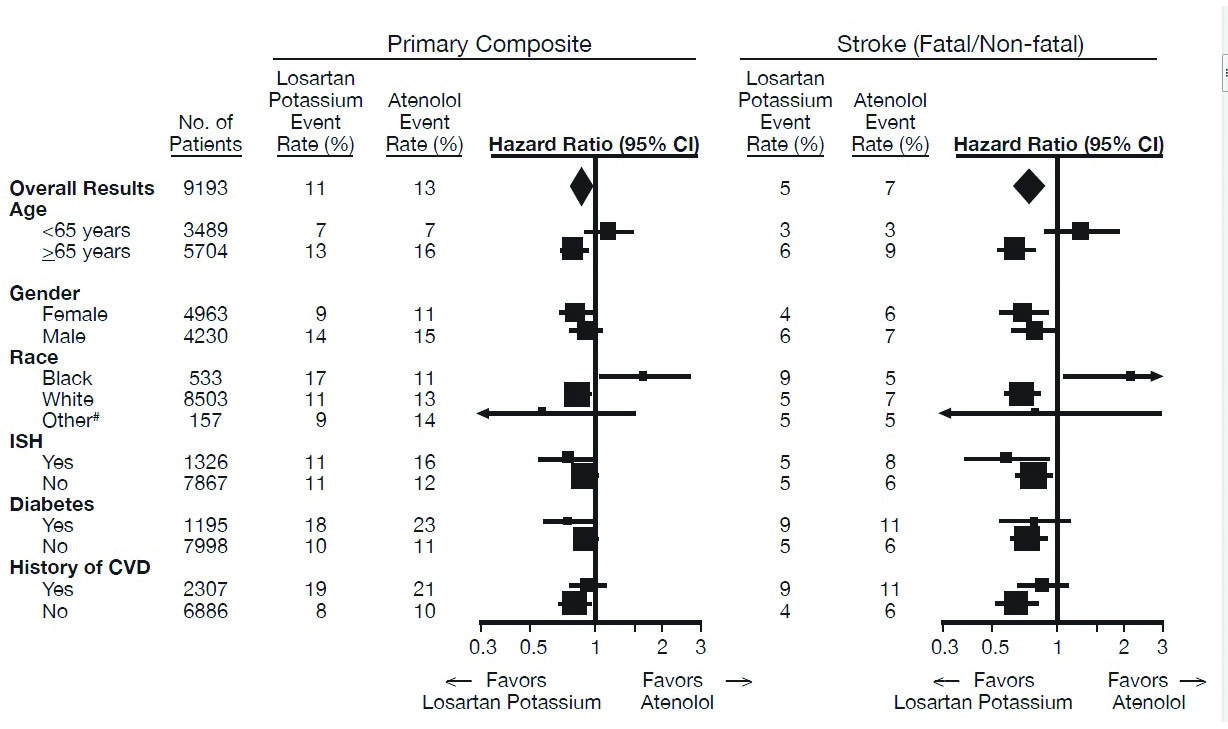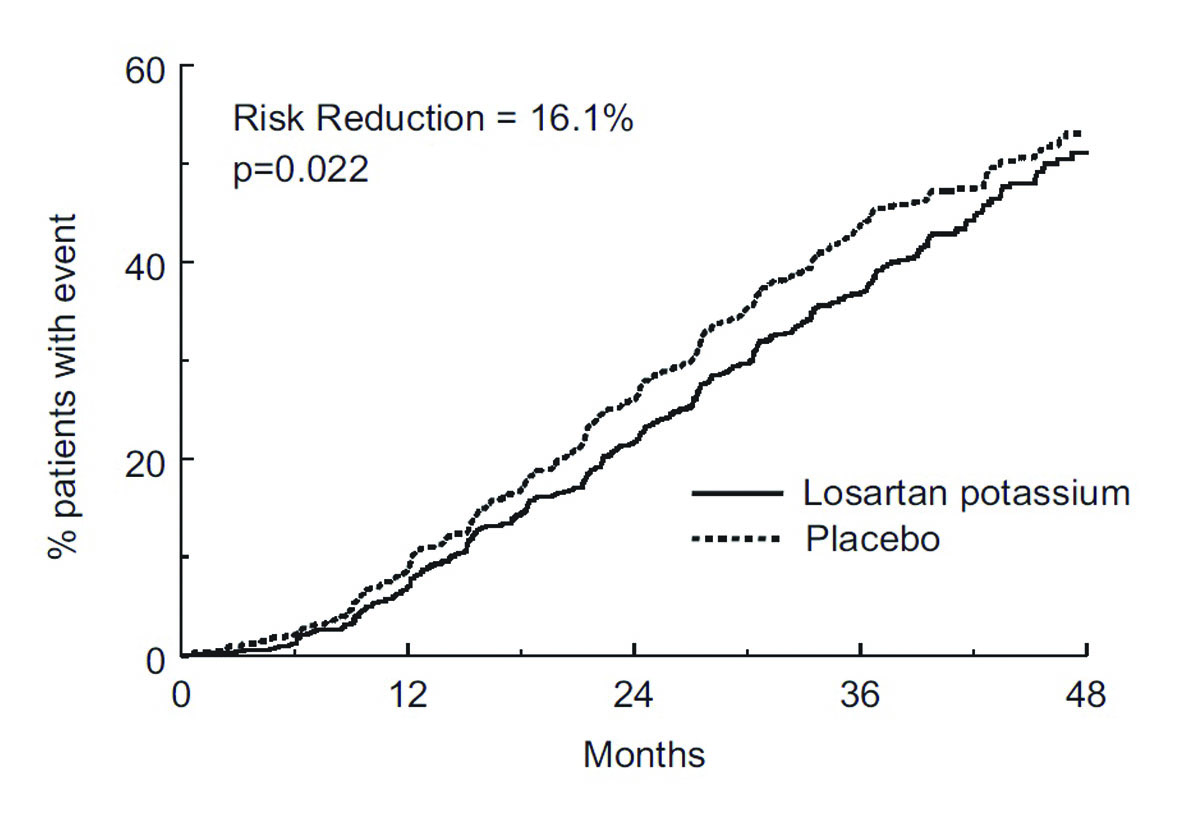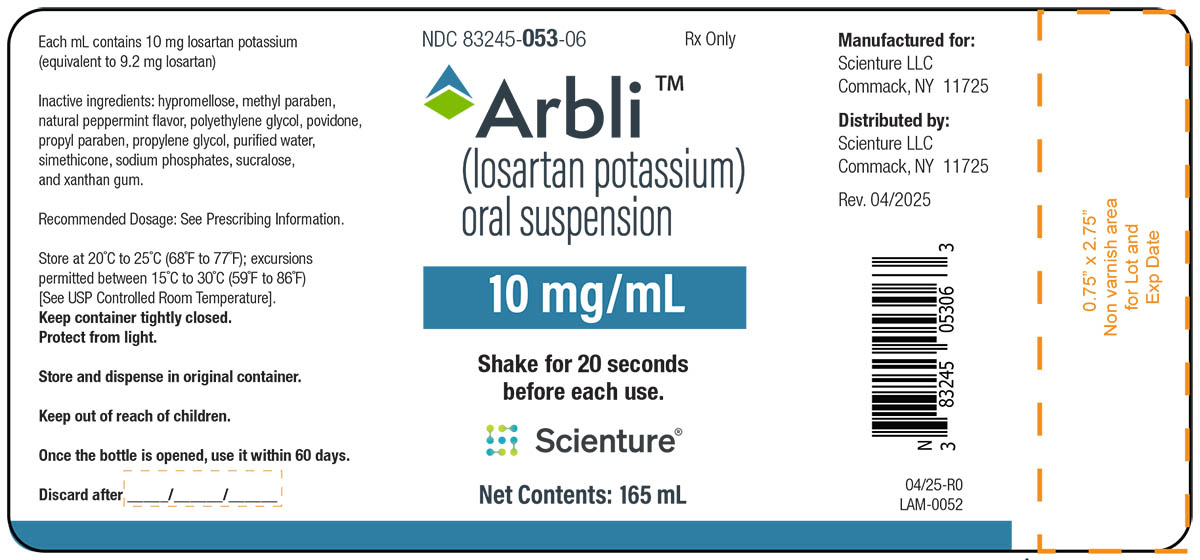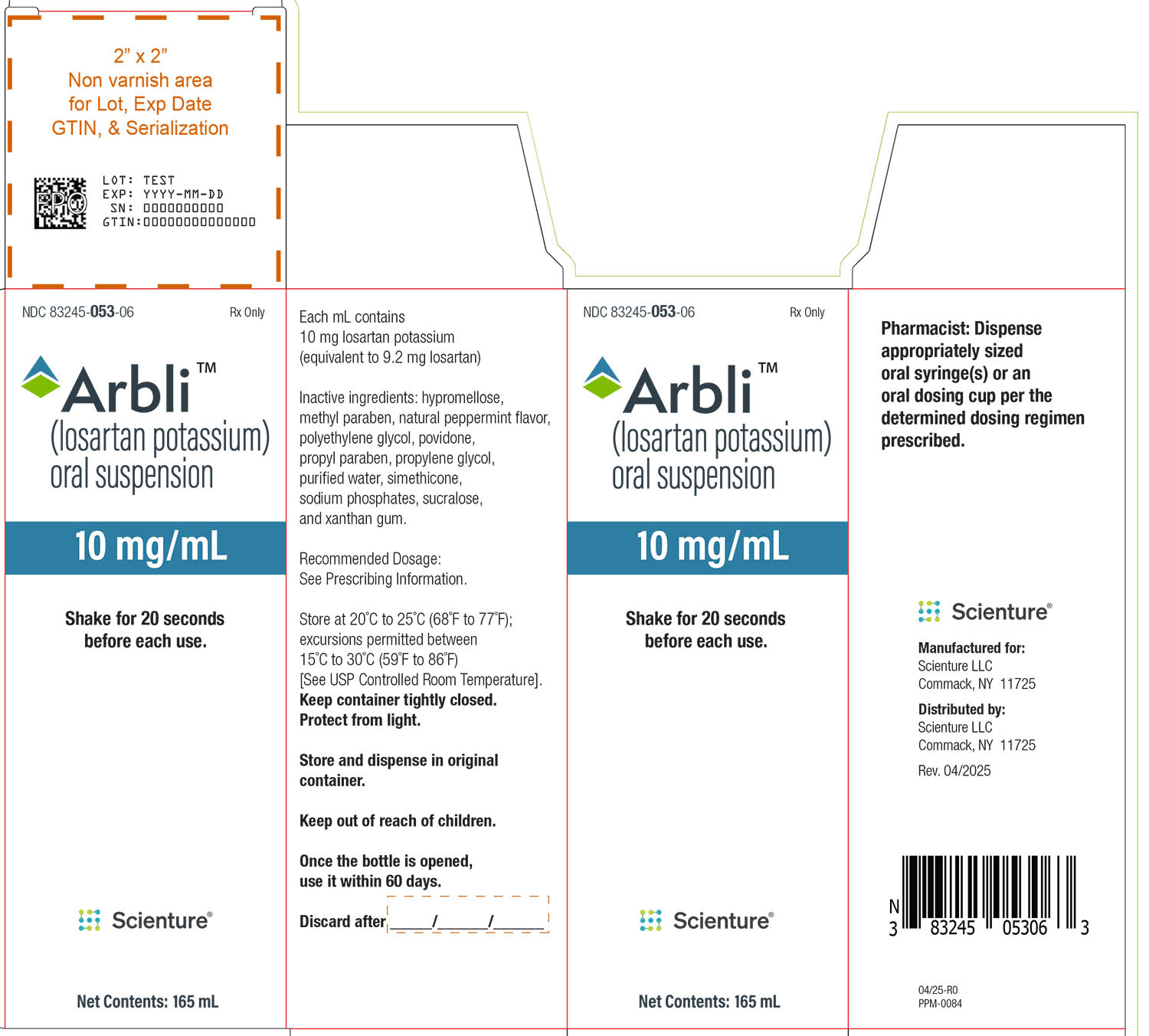 DRUG LABEL: ARBLI
NDC: 83245-053 | Form: SUSPENSION
Manufacturer: Scienture LLC
Category: prescription | Type: HUMAN PRESCRIPTION DRUG LABEL
Date: 20251003

ACTIVE INGREDIENTS: LOSARTAN POTASSIUM 10 mg/1 mL
INACTIVE INGREDIENTS: HYPROMELLOSES; METHYLPARABEN; PROPYLPARABEN; POLYETHYLENE GLYCOL 400; POVIDONE; PROPYLENE GLYCOL; WATER; DIMETHICONE; SUCRALOSE; XANTHAN GUM; SODIUM PHOSPHATE, DIBASIC; SODIUM PHOSPHATE, MONOBASIC; SILICON DIOXIDE

HIGHLIGHTS OF PRESCRIBING INFORMATION

These highlights do not include all the information needed to use ARBLI safely and effectively. See full prescribing information for ARBLI.
ARBLI (losartan potassium) oral suspension, for oral use
Initial U.S. Approval: 1995

WARNING: FETAL TOXICITY

See full prescribing information for complete boxed warning.

When pregnancy is detected, discontinue Arbli as soon as possible. Drugs that act directly on the renin-angiotensin system can cause injury and death to the developing fetus. (5.1)

1 INDICATIONS AND USAGE

Arbli is an angiotensin II receptor blocker (ARB) indicated for:

- Treatment of hypertension, to lower blood pressure in adults and children greater than 6 years old. Lowering blood pressure reduces the risk of fatal and nonfatal cardiovascular events, primarily strokes and myocardial infarctions. (1.1)
- Reduction of the risk of stroke in patients with hypertension and left ventricular hypertrophy. There is evidence that this benefit does not apply to Black patients. (1.2)
- Treatment of diabetic nephropathy with an elevated serum creatinine and proteinuria in patients with type 2 diabetes and a history of hypertension. (1.3)

2 DOSAGE AND ADMINISTRATION

Hypertension

- Usual adult dose: 50 mg orally once daily. (2.2)
- Usual pediatric starting dose: 0.7 mg per kg orally once daily (up to 50 mg). (2.2)

Hypertensive Patients with Left Ventricular Hypertrophy

- Usual starting dose: 50 mg orally once daily. (2.3)
- Add hydrochlorothiazide 12.5 mg and/or increase Arbli to 100 mg orally followed by an increase to hydrochlorothiazide 25 mg if further blood pressure response is needed. (2.3, 14.2)

Nephropathy in Type 2 Diabetic Patients

- Usual dose: 50 mg orally once daily. (2.4)
- Increase dose to 100 mg orally once daily if further blood pressure response is needed. (2.4)

3 DOSAGE FORMS AND STRENGTHS

Oral Suspension: 10 mg/mL. (3)

4 CONTRAINDICATIONS

- Hypersensitivity to any component. (4)
- Co-administration with aliskiren in patients with diabetes. (4)

5 WARNINGS AND PRECAUTIONS

- Hypotension: Correct volume or salt depletion prior to administration of Arbli. (5.2)
- Monitor renal function and potassium in susceptible patients. (5.3, 5.4)

6 ADVERSE REACTIONS

Most common adverse reactions (incidence ≥2% and greater than placebo) are: dizziness, upper respiratory infection, nasal congestion, and back pain. (6.1)

To report SUSPECTED ADVERSE REACTIONS, contact Scienture LLC at 1-833-754-4917 or FDA at 1-800-FDA-1088 or www.fda.gov/medwatch.

7 DRUG INTERACTIONS

- Agents Increasing Serum Potassium: Risk of hyperkalemia. (7.1)
- Lithium: Risk of lithium toxicity. (7.2)
- NSAIDs: Increased risk of renal impairment and reduced diuretic, natriuretic, and antihypertensive effects. (7.3)
- Dual Inhibition of the Renin-Angiotensin System: Increased risk of renal impairment, hypotension, syncope, and hyperkalemia. (7.4)

8 USE IN SPECIFIC POPULATIONS

- Lactation: Advise not to breastfeed during treatment with Arbli and for 2 days after the last dose (8.2).
- Arbli is not recommended in pediatric patients less than 2 years of age or in pediatric patients with glomerular filtration rate less than 30 mL/min/1.73 m^2. (2.2, 8.4)
- Hepatic Impairment: Recommended starting dose 25 mg once daily. (2.5, 8.8, 12.3)

FULL PRESCRIBING INFORMATION

WARNING: FETAL TOXICITY

When pregnancy is detected, discontinue Arbli as soon as possible. Drugs that act directly on the renin-angiotensin system can cause injury and death to the developing fetus [see Warnings and Precautions (5.1)].

1 INDICATIONS AND USAGE

1.1 Hypertension

Arbli is indicated for the treatment of hypertension in adults and pediatric patients 6 years of age and older, to lower blood pressure. Lowering blood pressure lowers the risk of fatal and nonfatal cardiovascular (CV) events, primarily strokes and myocardial infarction. These benefits have been seen in controlled trials of antihypertensive drugs from a wide variety of pharmacologic classes including losartan.

Control of high blood pressure should be part of comprehensive cardiovascular risk management, including, as appropriate, lipid control, diabetes management, antithrombotic therapy, smoking cessation, exercise, and limited sodium intake. Many patients will require more than 1 drug to achieve blood pressure goals. For specific advice on goals and management, see published guidelines, such as those of the National High Blood Pressure Education Program’s Joint National Committee on Prevention, Detection, Evaluation, and Treatment of High Blood Pressure (JNC).

Numerous antihypertensive drugs, from a variety of pharmacologic classes and with different mechanisms of action, have been shown in randomized controlled trials to reduce cardiovascular morbidity and mortality, and it can be concluded that it is blood pressure reduction, and not some other pharmacologic property of the drugs, that is largely responsible for those benefits. The largest and most consistent cardiovascular outcome benefit has been a reduction in the risk of stroke, but reductions in myocardial infarction and cardiovascular mortality also have been seen regularly.

Elevated systolic or diastolic pressure causes increased cardiovascular risk, and the absolute risk increase per mmHg is greater at higher blood pressures, so that even modest reductions of severe hypertension can provide substantial benefit. Relative risk reduction from blood pressure reduction is similar across populations with varying absolute risk, so the absolute benefit is greater in patients who are at higher risk independent of their hypertension (for example, patients with diabetes or hyperlipidemia), and such patients would be expected to benefit from more aggressive treatment to a lower blood pressure goal.

Some antihypertensive drugs have smaller blood pressure effects (as monotherapy) in Black patients, and many antihypertensive drugs have additional approved indications and effects (e.g., on angina, heart failure, or diabetic kidney disease). These considerations may guide selection of therapy.

Arbli may be administered with other antihypertensive agents.

1.2 Hypertensive Patients with Left Ventricular Hypertrophy

Arbli is indicated to reduce the risk of stroke in patients with hypertension and left ventricular hypertrophy, but there is evidence that this benefit does not apply to Black patients [see Use in Specific Populations (8.6) and Clinical Pharmacology (12.3)].

1.3 Nephropathy in Type 2 Diabetic Patients

Arbli is indicated for the treatment of diabetic nephropathy with an elevated serum creatinine and proteinuria (urinary albumin to creatinine ratio ≥300 mg/g) in patients with type 2 diabetes and a history of hypertension. In this population, Arbli reduces the rate of progression of nephropathy as measured by the occurrence of doubling of serum creatinine or end stage renal disease (need for dialysis or renal transplantation) [see Clinical Studies (14.3)].

2 DOSAGE AND ADMINISTRATION

2.1 Important Administration Information

Instruct patients or caregivers to use oral dosing syringe(s) or an oral dosing cup to measure the prescribed amount of medication. Inform patients that oral dosing syringe(s) or an oral dosing cup may be obtained from their pharmacy.

2.2 Hypertension

Adult Hypertension

The usual starting dose of Arbli is 50 mg orally once daily. The dosage can be increased to a maximum dose of 100 mg orally once daily as needed to control blood pressure [see Clinical Studies (14.1)]. A starting dose of 25 mg once daily is recommended for patients with possible intravascular depletion (e.g., on diuretic therapy).

Pediatric Hypertension

The usual recommended starting dose is 0.7 mg per kg orally once daily (up to 50 mg total) administered as a suspension. Dosage should be adjusted according to blood pressure response. Doses above 1.4 mg per kg (or in excess of 100 mg) daily have not been studied in pediatric patients [see Clinical Pharmacology (12.3), Clinical Studies (14.1), and Warnings and Precautions (5.2)].

Arbli is not recommended in pediatric patients less than 2 years of age or in pediatric patients with estimated glomerular filtration rate less than 30 mL/min/1.73 m^2 [see Use in Specific Populations (8.4), Clinical Pharmacology (12.3), and Clinical Studies (14)].

2.3 Hypertensive Patients with Left Ventricular Hypertrophy

The usual starting dose is 50 mg of Arbli orally once daily. Hydrochlorothiazide 12.5 mg daily should be added and/or the dose of Arbli should be increased to 100 mg orally once daily followed by an increase in hydrochlorothiazide to 25 mg once daily based on blood pressure response [see Clinical Studies (14.2)].

2.4 Nephropathy in Type 2 Diabetic Patients

The usual starting dose is 50 mg orally once daily. The dose should be increased to 100 mg orally once daily based on blood pressure response [see Clinical Studies (14.3)].

2.5 Dosage Modifications in Patients with Hepatic Impairment

In patients with mild-to-moderate hepatic impairment the recommended starting dose of Arbli is 25 mg orally once daily. Arbli has not been studied in patients with severe hepatic impairment [see Use in Specific Populations (8.8) and Clinical Pharmacology (12.3)].

3 DOSAGE FORMS AND STRENGTHS

- Arbli (losartan potassium) oral suspension, 10 mg/mL, is a white, translucent suspension with a peppermint odor.

4 CONTRAINDICATIONS

Arbli is contraindicated:

- In patients who are hypersensitive to any component of this product.
- For co-administration with aliskiren in patients with diabetes.

5 WARNINGS AND PRECAUTIONS

5.1 Fetal Toxicity

Arbli can cause fetal harm when administered to a pregnant woman. Use of drugs that act on the renin-angiotensin system during the second and third trimesters of pregnancy reduces fetal renal function and increases fetal and neonatal morbidity and death. Resulting oligohydramnios can be associated with fetal lung hypoplasia and skeletal deformations. Potential neonatal adverse effects include skull hypoplasia, anuria, hypotension, renal failure, and death. When pregnancy is detected, discontinue Arbli as soon as possible [see Use in Specific Populations (8.1)].

5.2 Hypotension in Volume-or Salt-Depleted Patients

In patients with an activated renin-angiotensin system, such as volume-or salt-depleted patients (e.g., those being treated with high doses of diuretics), symptomatic hypotension may occur after initiation of treatment with Arbli. Correct volume or salt depletion prior to administration of Arbli [see Dosage and Administration (2.2)].

5.3 Renal Function Deterioration

Changes in renal function including acute renal failure can be caused by drugs that inhibit the renin-angiotensin system and by diuretics. Patients whose renal function may depend in part on the activity of the renin-angiotensin system (e.g., patients with renal artery stenosis, chronic kidney disease, severe congestive heart failure, or volume depletion) may be at particular risk of developing acute renal failure on Arbli. Monitor renal function periodically in these patients. Consider withholding or discontinuing therapy in patients who develop a clinically significant decrease in renal function on Arbli [see Drug Interactions (7.3) and Use in Specific Populations (8.7)].

5.4 Hyperkalemia

Monitor serum potassium periodically and treat appropriately. Dosage reduction or discontinuation of Arbli may be required [see Adverse Reactions (6.1)].

Concomitant use of other drugs that may increase serum potassium may lead to hyperkalemia [see Drug Interactions (7.1)].

6 ADVERSE REACTIONS

6.1 Clinical Trials Experience

Because clinical trials are conducted under widely varying conditions, adverse reaction rates observed in the clinical trials of a drug cannot be directly compared to rates in the clinical trials of another drug and may not reflect the rates observed in practice.

Hypertension

Arbli has been evaluated for safety in more than 3,300 adult patients treated for essential hypertension and 4058 patients/subjects overall. Over 1,200 patients were treated for over 6 months and more than 800 for over one year.

Treatment with Arbli was well-tolerated with an overall incidence of adverse events similar to that of placebo. In controlled clinical trials, discontinuation of therapy for adverse events occurred in 2.3% of patients treated with Arbli and 3.7% of patients given placebo. In 4 clinical trials involving over 1,000 patients on various doses (10 mg to 150 mg) of losartan potassium and over 300 patients given placebo, the adverse events that occurred in ≥2% of patients treated with Arbli and more commonly than placebo were: dizziness (3% vs. 2%), upper respiratory infection (8% vs. 7%), nasal congestion (2% vs. 1%), and back pain (2% vs. 1%).

The following less common adverse reactions have been reported:

Blood and lymphatic system disorders: Anemia.

Psychiatric disorders: Depression.

Nervous system disorders: Somnolence, headache, sleep disorders, paresthesia, migraine.

Ear and labyrinth disorders: Vertigo, tinnitus.

Cardiac disorders: Palpitations, syncope, atrial fibrillation, CVA.

Respiratory, thoracic and mediastinal disorders: Dyspnea.

Gastrointestinal disorders: Abdominal pain, constipation, nausea, vomiting.

Skin and subcutaneous tissue disorders: Urticaria, pruritus, rash, photosensitivity.

Musculoskeletal and connective tissue disorders: Myalgia, arthralgia.

Reproductive system and breast disorders: Impotence.

General disorders and administration site conditions: Edema.

Cough

Persistent dry cough (with an incidence of a few percent) has been associated with ACE-inhibitor use and in practice can be a cause of discontinuation of ACE-inhibitor therapy. Two prospective, parallel-group, double-blind, randomized, controlled trials were conducted to assess the effects of losartan on the incidence of cough in hypertensive patients who had experienced cough while receiving ACE-inhibitor therapy. Patients who had typical ACE-inhibitor cough when challenged with lisinopril, whose cough disappeared on placebo, were randomized to losartan 50 mg, lisinopril 20 mg, or either placebo (one study, n=97) or 25 mg hydrochlorothiazide (n=135). The double-blind treatment period lasted up to 8 weeks. The incidence of cough is shown in Table 1 below.

Table 1

Study 1* | HCTZ | Losartan | Lisinopril
Cough | 25% | 17% | 69%
Study 2† | Placebo | Losartan | Lisinopril
Cough | 35% | 29% | 62%

* Demographics = (89% Caucasian, 64% female)

† Demographics = (90% Caucasian, 51% female)

These studies demonstrate that the incidence of cough associated with losartan therapy, in a population that all had cough associated with ACE-inhibitor therapy, is similar to that associated with hydrochlorothiazide or placebo therapy.

Cases of cough, including positive re-challenges, have been reported with the use of losartan in postmarketing experience.

Hypertensive Patients with Left Ventricular Hypertrophy

In the Losartan Intervention for Endpoint (LIFE) study, adverse reactions with losartan were similar to those reported previously for patients with hypertension.

Nephropathy in Type 2 Diabetic Patients

In the Reduction of Endpoints in NIDDM with the Angiotensin II Receptor Antagonist Losartan (RENAAL) study involving 1,513 patients treated with losartan or placebo, the overall incidences of reported adverse events were similar for the two groups. Discontinuations of losartan because of side effects were similar to placebo (19% for losartan, 24% for placebo). The adverse events, regardless of drug relationship, reported with an incidence of ≥4% of patients treated with losartan and occurring with ≥2% difference in the losartan group vs. placebo on a background of conventional antihypertensive therapy, were asthenia/fatigue, chest pain, hypotension, orthostatic hypotension, diarrhea, anemia, hyperkalemia, hypoglycemia, back pain, muscular weakness, and urinary tract infection.

6.2 Postmarketing Experience

The following additional adverse reactions have been reported in postmarketing experience with losartan.

Because these reactions are reported voluntarily from a population of uncertain size, it is not always possible to estimate their frequency reliably or to establish a causal relationship to drug exposure:

Digestive: Hepatitis.

General Disorders and Administration Site Conditions: Malaise.

Hematologic: Thrombocytopenia.

Hypersensitivity: Angioedema, including swelling of the larynx and glottis, causing airway obstruction and/or swelling of the face, lips, pharynx, tongue, and/or swelling of the intestine has been reported; some of these patients previously experienced angioedema with other drugs including ACE inhibitors. Vasculitis, including Henoch-Schönlein purpura, has been reported. Anaphylactic reactions have been reported.

Metabolic and Nutrition: Hyponatremia.

Musculoskeletal: Rhabdomyolysis.

Nervous System Disorders: Dysgeusia.

Skin: Erythroderma.

7 DRUG INTERACTIONS

7.1 Agents Increasing Serum Potassium

Co-administration of losartan with other drugs that raise serum potassium levels may result in hyperkalemia. Monitor serum potassium in such patients.

7.2 Lithium

Increases in serum lithium concentrations and lithium toxicity have been reported during concomitant administration of lithium with angiotensin II receptor antagonists. Monitor serum lithium levels during concomitant use.

7.3 Non-Steroidal Anti-Inflammatory Drugs (NSAIDs) Including Selective Cyclooxygenase-2 Inhibitors (COX-2 Inhibitors)

In patients who are elderly, volume-depleted (including those on diuretic therapy), or with compromised renal function, co-administration of NSAIDs, including selective COX-2 inhibitors, with angiotensin II receptor antagonists (including losartan) may result in deterioration of renal function, including possible acute renal failure. These effects are usually reversible. Monitor renal function periodically in patients receiving losartan and NSAID therapy.

The antihypertensive effect of angiotensin II receptor antagonists, including losartan, may be attenuated by NSAIDs, including selective COX-2 inhibitors.

7.4 Dual Blockade of the Renin-Angiotensin System (RAS)

Dual blockade of the RAS with angiotensin receptor blockers, ACE inhibitors, or aliskiren is associated with increased risks of hypotension, syncope, hyperkalemia, and changes in renal function (including acute renal failure) compared to monotherapy.

The Veterans Affairs Nephropathy in Diabetes (VA NEPHRON-D) trial enrolled 1,448 patients with type 2 diabetes, elevated urinary-albumin-to-creatinine ratio, and decreased estimated glomerular filtration rate (GFR 30 to 89.9 mL/min), randomized them to lisinopril or placebo on a background of losartan therapy and followed them for a median of 2.2 years. Patients receiving the combination of losartan and lisinopril did not obtain any additional benefit compared to monotherapy for the combined endpoint of decline in GFR, end stage renal disease, or death, but experienced an increased incidence of hyperkalemia and acute kidney injury compared with the monotherapy group.

In most patients no benefit has been associated with using two RAS inhibitors concomitantly. In general, avoid combined use of RAS inhibitors. Closely monitor blood pressure, renal function, and electrolytes in patients on losartan and other agents that affect the RAS.

Do not co-administer aliskiren with losartan in patients with diabetes. Avoid use of aliskiren with losartan in patients with renal impairment (GFR <60 mL/min).

8 USE IN SPECIFIC POPULATIONS

8.1 Pregnancy

Risk Summary

Arbli can cause fetal harm when administered to a pregnant woman. Use of drugs that act on the renin-angiotensin system during the second and third trimesters of pregnancy reduces fetal renal function and increases fetal and neonatal morbidity and death (see Clinical Considerations). Most epidemiologic studies examining fetal abnormalities after exposure to antihypertensive use in the first trimester have not distinguished drugs affecting the renin-angiotensin system from other antihypertensive agents. When pregnancy is detected, discontinue losartan as soon as possible.

The estimated background risk of major birth defects and miscarriage for the indicated population is unknown. All pregnancies have a background risk of birth defect, loss, or other adverse outcomes. In the

U.S. general population, the estimated background risk of major birth defects and miscarriage in clinically recognized pregnancies is 2% to 4% and 15% to 20%, respectively.

Clinical Considerations

Disease-associated Maternal and/or Embryo/Fetal Risk

Hypertension in pregnancy increases the maternal risk for pre-eclampsia, gestational diabetes, premature delivery, and delivery complications (e.g., need for cesarean section, post-partum hemorrhage). Hypertension increases the fetal risk for intrauterine growth restriction and intrauterine death. Pregnant women with hypertension should be carefully monitored and managed accordingly.

Fetal/Neonatal Adverse Reactions

Oligohydramnios in pregnant women who use drugs affecting the renin-angiotensin system in the second and third trimesters of pregnancy can result in the following: reduced fetal renal function leading to anuria and renal failure, fetal lung hypoplasia, skeletal deformations, including skull hypoplasia, hypotension, and death. In the unusual case that there is no appropriate alternative to therapy with drugs affecting the renin-angiotensin system for a particular patient, apprise the mother of the potential risk to the fetus.

In patients taking losartan during pregnancy, perform serial ultrasound examinations to assess the intra-amniotic environment. Fetal testing may be appropriate, based on the week of gestation. If oligohydramnios is observed, discontinue losartan, unless it is considered lifesaving for the mother. Patients and physicians should be aware, however, that oligohydramnios may not appear until after the fetus has sustained irreversible injury.

Closely observe neonates with histories of in utero exposure to losartan for hypotension, oliguria, and hyperkalemia. In neonates with a history of in utero exposure to losartan, if oliguria or hypotension occurs, support blood pressure and renal perfusion. Exchange transfusions or dialysis may be required as a means of reversing hypotension and replacing renal function.

Data

Animal Data

Losartan potassium was administered orally to rats during the period of late gestation through lactation (Gestation Day 15 through Lactation Day 20) at doses of 10, 25, and 100 mg/kg/day. Losartan potassium has been shown to produce adverse effects in rat fetuses and neonates, including decreased body weight, delayed physical and behavioral development, mortality and renal toxicity. With the exception of neonatal weight gain (which was affected at doses as low as 10 mg/kg/day), doses associated with these effects exceeded 25 mg/kg/day (approximately three times the maximum recommended human dose of 100 mg on a mg/m^2 basis). These findings are attributed to drug exposure in late gestation and during lactation. Significant levels of losartan and its active metabolite were shown to be present in rat fetal plasma during late gestation and in rat milk.

8.2 Lactation

Risk Summary

It is not known whether losartan is present in human milk, but significant levels of losartan and its active metabolite were shown to be present in rat milk Because of the potential for serious adverse reactions in breastfed infants, advise a lactating woman that breastfeeding is not recommended during the treatment with losartan and for 2 days after the last dose.

8.4 Pediatric Use

Antihypertensive effects of Arbli have been established in hypertensive pediatric patients aged 6 to 16 years. Safety and effectiveness have not been established in pediatric patients under the age of 6 or in pediatric patients with glomerular filtration rate <30 mL/min/1.73 m^2 [see Dosage and Administration (2.1), Clinical Pharmacology (12.3), and Clinical Studies (14.1)]. Use of Arbli is not recommended in children less than 2 years of age. It is not known whether post-natal use of losartan, before maturation of renal function is complete, has a longterm deleterious effect on the kidney.

8.5 Geriatric Use

Of the total number of patients receiving Arbli in controlled clinical studies for hypertension, 391 patients (19%) were 65 years and over, while 37 patients (2%) were 75 years and over. In a controlled clinical study for renal protection in type 2 diabetic patients with proteinuria, 248 patients (33%) were 65 years and over. In a controlled clinical study for the reduction in the combined risk of cardiovascular death, stroke and myocardial infarction in hypertensive patients with left ventricular hypertrophy, 2,857 patients (62%) were 65 years and over, while 808 patients (18%) were 75 years and over. No overall differences in effectiveness or safety were observed between these patients and younger patients, but greater sensitivity of some older individuals cannot be ruled out.

8.6 Race

In the LIFE study, Black patients with hypertension and left ventricular hypertrophy treated with atenolol were at lower risk of experiencing the primary composite endpoint compared with Black patients treated with losartan (both cotreated with hydrochlorothiazide in the majority of patients). The primary endpoint was the first occurrence of stroke, myocardial infarction or cardiovascular death, analyzed using an intention-to-treat (ITT) approach. In the subgroup of Black patients (n=533, 6% of the LIFE study patients), there were 29 primary endpoints among 263 patients on atenolol (11%, 26 per 1,000 patient-years) and 46 primary endpoints among 270 patients (17%, 42 per 1,000 patient-years) on losartan. This finding could not be explained on the basis of differences in the populations other than race or on any imbalances between treatment groups. In addition, blood pressure reductions in both treatment groups were consistent between Black and non-Black patients. Given the difficulty in interpreting subset differences in large trials, it cannot be known whether the observed difference is the result of chance. However, the LIFE study provides no evidence that the benefits of losartan on reducing the risk of cardiovascular events in hypertensive patients with left ventricular hypertrophy apply to Black patients [see Clinical Studies (14.2)].

8.7 Renal Impairment

Patients with renal insufficiency have elevated plasma concentrations of losartan and its active metabolite compared to subjects with normal renal function. No dose adjustment is necessary in patients with renal impairment unless a patient with renal impairment is also volume depleted [see Dosage and Administration (2.4), Warnings and Precautions (5.3) and Clinical Pharmacology (12.3)].

8.8 Hepatic Impairment

The recommended starting dose of losartan is 25 mg in patients with mild-to-moderate hepatic impairment. Following oral administration in patients with mild-to-moderate hepatic impairment, plasma concentrations of losartan and its active metabolite were, respectively, 5 times and 1.7 times those seen in healthy volunteers. losartan has not been studied in patients with severe hepatic impairment [see Dosage and Administration (2.5) and Clinical Pharmacology (12.3)].

10 OVERDOSAGE

Significant lethality was observed in mice and rats after oral administration of 1,000 mg/kg and 2,000 mg/kg, respectively, about 44 and 170 times the maximum recommended human dose on a mg/m^2 basis.

Limited data are available in regard to overdosage in humans. The most likely manifestation of overdosage would be hypotension and tachycardia; bradycardia could occur from parasympathetic (vagal) stimulation. If symptomatic hypotension should occur, supportive treatment should be instituted.

Neither losartan nor its active metabolite can be removed by hemodialysis.

11 DESCRIPTION

Losartan potassium is an angiotensin II receptor blocker acting on the AT1 receptor subtype. Losartan potassium, a non-peptide molecule, is chemically described as 2-butyl-4-chloro-1-[p-(o-1H-tetrazol-5-ylphenyl)benzyl]imidazole-5-methanol monopotassium salt.

Its empirical formula is C22H22ClKN6O, and its structural formula is:

Losartan potassium is a white to off-white free-flowing crystalline powder with a molecular weight of 461.01. It is freely soluble in water, soluble in alcohols, and slightly soluble in common organic solvents, such as acetonitrile and methyl ethyl ketone. Oxidation of the 5-hydroxymethyl group on the imidazole ring results in the active metabolite of losartan.

Arbli is available as a white, translucent oral suspension with a peppermint odor. Each mL contains 10 mg losartan potassium (equivalent to 9.2 mg losartan), inactive ingredients are: hypromellose, methyl paraben, natural peppermint flavor, polyethylene glycol, povidone, propyl paraben, propylene glycol, purified water, simethicone, sodium phosphates, sucralose, and xanthan gum.

12 CLINICAL PHARMACOLOGY

12.1 Mechanism of Action

Angiotensin II [formed from angiotensin I in a reaction catalyzed by angiotensin converting enzyme (ACE, kininase II)] is a potent vasoconstrictor, the primary vasoactive hormone of the renin-angiotensin system, and an important component in the pathophysiology of hypertension. It also stimulates aldosterone secretion by the adrenal cortex. Losartan and its principal active metabolite block the vasoconstrictor and aldosterone-secreting effects of angiotensin II by selectively blocking the binding of angiotensin II to the AT1 receptor found in many tissues, (e.g., vascular smooth muscle, adrenal gland). There is also an AT2 receptor found in many tissues, but it is not known to be associated with cardiovascular homeostasis.

Neither losartan nor its principal active metabolite exhibits any partial agonist activity at the AT1 receptor, and both have much greater affinity (about 1,000-fold) for the AT1 receptor than for the AT2 receptor. In vitro binding studies indicate that losartan is a reversible, competitive inhibitor of the AT1 receptor. The active metabolite is 10 to 40 times more potent by weight than losartan and appears to be a reversible, noncompetitive inhibitor of the AT1 receptor.

Neither losartan nor its active metabolite inhibits ACE (kininase II, the enzyme that converts angiotensin I to angiotensin II and degrades bradykinin), nor do they bind to or block other hormone receptors or ion channels known to be important in cardiovascular regulation.

12.2 Pharmacodynamics

Losartan inhibits the pressor effect of angiotensin II (as well as angiotensin I) infusions. A dose of 100 mg inhibits the pressor effect by about 85% at peak with 25% to 40% inhibition persisting for 24 hours. Removal of the negative feedback of angiotensin II causes a doubling to tripling in plasma renin activity and consequent rise in angiotensin II plasma concentration in hypertensive patients. Losartan does not affect the response to bradykinin, whereas ACE inhibitors increase the response to bradykinin. Aldosterone plasma concentrations fall following losartan administration. In spite of the effect of losartan on aldosterone secretion, very little effect on serum potassium was observed.

The effect of losartan is substantially present within one week, but in some studies the maximal effect occurred in 3 to 6 weeks. In long-term follow-up studies (without placebo control), the effect of losartan appeared to be maintained for up to a year. There is no apparent rebound effect after abrupt withdrawal of losartan. There was essentially no change in average heart rate in losartan-treated patients in controlled trials.

12.3 Pharmacokinetics

Absorption

Following oral administration, losartan is well absorbed and undergoes substantial first-pass metabolism. The systemic bioavailability of losartan is approximately 33%. Mean peak concentrations of losartan and its active metabolite are reached in 1 hour and in 2 hours, respectively. While maximum plasma concentrations of losartan and its active metabolite are approximately equal, the AUC (area under the curve) of the metabolite is about 4 times as great as that of losartan. The pharmacokinetics of losartan and its active metabolite are linear with oral losartan doses up to 200 mg and do not change over time.

Effect of food

A high-fat high-calorie meal (937 calories, 56% fat) slows absorption of losartan and decreases the Cmax of losartan and its active metabolite but has only minor effects on the AUC of losartan and its active metabolite.

Distribution

The volume of distribution of losartan and the active metabolite is about 34 liters and 12 liters, respectively. Both losartan and its active metabolite are highly bound to plasma proteins, primarily albumin, with plasma free fractions of 1.3% and 0.2%, respectively. Plasma protein binding is constant over the concentration range achieved with recommended doses. Studies in rats indicate that losartan crosses the blood-brain barrier poorly, if at all.

Elimination

Total plasma clearance of losartan and the active metabolite is about 600 mL/min and 50 mL/min, respectively, with renal clearance of about 75 mL/min and 25 mL/min, respectively. The terminal half-life of losartan and the active metabolite is about 2 hours and about 6 hours, respectively. Neither losartan nor its metabolite accumulates in plasma upon repeated once-daily dosing.

Metabolism

Losartan is an orally active agent that undergoes substantial first-pass metabolism by cytochrome P450 enzymes. It is converted, in part, to an active carboxylic acid metabolite that is responsible for most of the angiotensin II receptor antagonism that follows losartan treatment. About 14% of an orally-administered dose of losartan is converted to the active metabolite. In addition to the active carboxylic acid metabolite, several inactive metabolites are formed. In vitro studies indicate that cytochrome P450 2C9 and 3A4 are involved in the biotransformation of losartan to its metabolites.

Excretion

After single doses of losartan administered orally, about 4% of the dose is excreted unchanged in the urine and about 6% is excreted in urine as the active metabolite. Biliary excretion contributes to the elimination of losartan and its metabolites. Following oral ^14C-labeled losartan, about 35% of radioactivity is recovered in the urine and about 60% in the feces. Following an intravenous dose of ^14C-labeled losartan, about 45% of radioactivity is recovered in the urine and 50% in the feces.

Specific Populations

Geriatric Patients

Losartan pharmacokinetics have been investigated in the elderly (65 to 75 years). Plasma concentrations of losartan and its active metabolite are similar in elderly and young hypertensives. No dosage adjustment is necessary [see Dosage and Administration (2.2)].

Pediatric Patients

Pharmacokinetic parameters after multiple doses of losartan (average dose 0.7 mg/kg, range

0.36 to 0.97 mg/kg) to 25 hypertensive patients aged 6 to 16 years are shown in Table 2 below. Pharmacokinetics of losartan and its active metabolite were generally similar across the studied age groups and similar to historical pharmacokinetic data in adults. The principal pharmacokinetic parameters in adults and children are shown in the table below.

Table 2: Pharmacokinetic Parameters in Hypertensive Adults and Children Age 6 to 16 Following Multiple Dosing

 | Adults given 50 mg once daily for; 7 days; N=12 |  | Age 6 to 16 given 0.7 mg/kg once daily for 7 days; N=25
 | Parent | Active Metabolite | Parent | Active Metabolite
AUC0-24 (ng•hr/mL)* | 442 ± 173 | 1685 ± 452 | 368 ± 169 | 1866 ± 1076
Cmax (ng/mL)* | 224 ± 82 | 212 ± 73 | 141 ± 88 | 222 ± 127
T1/2 (h)† | 2.1 ± 0.70 | 7.4 ± 2.4 | 2.3 ± 0.8 | 5.6 ± 1.2
TPEAK (h)‡ | 0.9 | 3.5 | 2.0 | 4.1
CLREN (mL/min)* | 56 ± 23 | 20 ± 3 | 53 ± 33 | 17 ± 8

* Mean ± standard deviation

† Harmonic mean and standard deviation

‡ Median

Male and Female Patients

Losartan pharmacokinetics have been investigated in males and females. Plasma concentrations of losartan were about twice as high in female hypertensives as male hypertensives, but concentrations of the active metabolite were similar in males and females. No dosage adjustment is necessary [see Dosage and Administration (2.2)].

Racial or Ethnic Groups

Pharmacokinetic differences due to race have not been studied [see Use in Specific Populations (8.6)].

Patients with Renal Impairment

Following oral administration, plasma concentrations and AUCs of losartan and its active metabolite are increased by 50% to 90% in patients with mild (creatinine clearance of 50 to 74 mL/min) or moderate (creatinine clearance 30 to 49 mL/min) renal insufficiency. Renal clearance was reduced by 55% to 85% for both losartan and its active metabolite in patients with mild or moderate renal insufficiency. Neither losartan nor its active metabolite can be removed by hemodialysis [see Warnings and Precautions (5.3) andUse in Specific Populations (8.7)].

Patients with Hepatic Impairment

Following oral administration in patients with mild to moderate alcoholic cirrhosis of the liver, plasma concentrations of losartan and its active metabolite were, respectively, 5-times and about 1.7-times those in young male volunteers. Compared to normal subjects, the total plasma clearance of losartan in patients with hepatic insufficiency was about 50% lower and the oral bioavailability was about doubled. Use a starting dose of 25 mg for patients with mild to moderate hepatic impairment. Losartan has not been studied in patients with severe hepatic impairment [see Dosage and Administration (2.5) andUse in Specific Populations (8.8)].

Drug Interactions

No clinically significant drug interactions have been found in studies of losartan potassium with hydrochlorothiazide, digoxin, warfarin, cimetidine, and phenobarbital. However, rifampin has been shown to decrease the AUC of losartan and its active metabolite by 30% and 40%, respectively. Fluconazole, an inhibitor of cytochrome P450 2C9, decreased the AUC of the active metabolite by approximately 40%, but increased the AUC of losartan by approximately 70% following multiple doses. Conversion of losartan to its active metabolite after intravenous administration is not affected by ketoconazole, an inhibitor of P450 3A4. The AUC of active metabolite following oral losartan was not affected by erythromycin, an inhibitor of P450 3A4, but the AUC of losartan was increased by 30%.

The pharmacodynamic consequences of concomitant use of losartan and inhibitors of P450 2C9 have not been examined. Subjects who do not metabolize losartan to active metabolite have been shown to have a specific, rare defect in cytochrome P450 2C9. These data suggest that the conversion of losartan to its active metabolite is mediated primarily by P450 2C9 and not P450 3A4.

13 NONCLINICAL TOXICOLOGY

13.1 Carcinogenesis and Mutagenesis and Impairment of Fertility

Losartan potassium was not carcinogenic when administered at maximally tolerated dosages to rats and mice for 105 and 92 weeks, respectively. Female rats given the highest dose (270 mg/kg/day) had a slightly higher incidence of pancreatic acinar adenoma. The maximally tolerated dosages (270 mg/kg/day in rats, 200 mg/kg/day in mice) provided systemic exposures for losartan and its pharmacologically active metabolite that were approximately 160 and 90 times (rats) and 30 and 15 times (mice) the exposure of a 50 kg human given 100 mg per day.

Losartan potassium was negative in the microbial mutagenesis and V-79 mammalian cell mutagenesis assays and in the in vitro alkaline elution and in vitro and in vivo chromosomal aberration assays. In addition, the active metabolite showed no evidence of genotoxicity in the microbial mutagenesis, in vitro alkaline elution, and in vitro chromosomal aberration assays.

Fertility and reproductive performance were not affected in studies with male rats given oral doses of losartan potassium up to approximately 150 mg/kg/day. The administration of toxic dosage levels in females (300/200 mg/kg/day) was associated with a significant (p<0.05) decrease in the number of corpora lutea/female, implants/female, and live fetuses/female at C-section. At 100 mg/kg/day only a decrease in the number of corpora lutea/female was observed. The relationship of these findings to drug-treatment is uncertain since there was no effect at these dosage levels on implants/pregnant female, percent post-implantation loss, or live animals/litter at parturition. In nonpregnant rats dosed at 135 mg/kg/day for 7 days, systemic exposure (AUCs) for losartan and its active metabolite were approximately 66 and 26 times the exposure achieved in man at the maximum recommended human daily dosage (100 mg).

14 CLINICAL STUDIES

14.1 Hypertension

Adult Hypertension

The antihypertensive effects of losartanwere demonstrated principally in 4 placebo-controlled, 6-to-12-week trials of dosages from 10 to 150 mg per day in patients with baseline diastolic blood pressures of 95 to 115. The studies allowed comparisons of two doses (50 to 100 mg/day) as once-daily or twice-daily regimens, comparisons of peak and trough effects, and comparisons of response by gender, age, and race. Three additional studies examined the antihypertensive effects of losartan and hydrochlorothiazide in combination.

The 4 studies of losartan monotherapy included a total of 1,075 patients randomized to several doses of losartan and 334 to placebo. The 10-and 25-mg doses produced some effect at peak (6 hours after dosing) but small and inconsistent trough (24 hour) responses. Doses of 50, 100 and 150 mg once daily gave statistically significant systolic/diastolic mean decreases in blood pressure, compared to placebo in the range of 5.5 to 10.5/3.5 to 7.5 mmHg, with the 150-mg dose giving no greater effect than 50 mg to 100 mg. Twice-daily dosing at 50 to 100 mg/day gave consistently larger trough responses than once-daily dosing at the same total dose. Peak (6 h) effects were uniformly, but moderately, larger than trough effects, with the trough-to-peak ratio for systolic and diastolic responses 50% to 95% and 60% to 90%, respectively.

Addition of a low dose of hydrochlorothiazide (12.5 mg) to losartan 50 mg once daily resulted in placebo-adjusted blood pressure reductions of 15.5/9.2 mmHg.

Analysis of age, gender, and race subgroups of patients showed that men and women, and patients over and under 65, had generally similar responses. Losartan was effective in reducing blood pressure regardless of race, although the effect was somewhat less in Black patients (usually a low-renin population).

Pediatric Hypertension

The antihypertensive effect of losartan was studied in one trial enrolling 177 hypertensive pediatric patients aged 6 to 16 years old. Children who weighed <50 kg received 2.5, 25 or 50 mg of losartan daily and patients who weighed ≥50 kg received 5, 50 or 100 mg of losartan daily. Children in the lowest dose group were given losartan in a suspension formulation [see Dosage and Administration (2.2)]. The majority of the children had hypertension associated with renal and urogenital disease. The sitting diastolic blood pressure (SiDBP) on entry into the study was higher than the 95th percentile level for the patient’s age, gender, and height. At the end of three weeks, losartan reduced systolic and diastolic blood pressure, measured at trough, in a dose-dependent manner. Overall, the two higher doses (25 to 50 mg in patients <50 kg; 50 to 100 mg in patients ≥50 kg) reduced diastolic blood pressure by 5 to 6 mmHg more than the lowest dose used (2.5 mg in patients <50 kg; 5 mg in patients ≥50 kg). The lowest dose, corresponding to an average daily dose of 0.07 mg/kg, did not appear to offer consistent antihypertensive efficacy. When patients were randomized to continue losartan at the two higher doses or to placebo after 3 weeks of therapy, trough diastolic blood pressure rose in patients on placebo between 5 and 7 mmHg more than patients randomized to continuing losartan. When the low dose of losartan was randomly withdrawn, the rise in trough diastolic blood pressure was the same in patients receiving placebo and in those continuing losartan, again suggesting that the lowest dose did not have significant antihypertensive efficacy. Overall, no significant differences in the overall antihypertensive effect of losartan were detected when the patients were analyzed according to age (<, ≥12 years old) or gender. While blood pressure was reduced in all racial subgroups examined, too few non-White patients were enrolled to compare the dose-response of losartan in the non-White subgroup.

14.2 Hypertensive Patients with Left Ventricular Hypertrophy

The LIFE study was a multinational, double-blind study comparing losartan and atenolol in 9,193 hypertensive patients with ECG-documented left ventricular hypertrophy. Patients with myocardial infarction or stroke within six months prior to randomization were excluded. Patients were randomized to receive once daily losartan50 mg or atenolol 50 mg. If goal blood pressure (<140/90 mmHg) was not reached, hydrochlorothiazide (12.5 mg) was added first and, if needed, the dose of losartan or atenolol was then increased to 100 mg once daily. If necessary, other antihypertensive treatments (e.g., increase in dose of hydrochlorothiazide therapy to 25 mg or addition of other diuretic therapy, calcium-channel blockers, alpha-blockers, or centrally acting agents, but not ACE inhibitors, angiotensin II antagonists, or beta-blockers) were added to the treatment regimen to reach the goal blood pressure.

Of the randomized patients, 4,963 (54%) were female and 533 (6%) were Black. The mean age was 67 with 5,704 (62%) age ≥65. At baseline, 1,195 (13%) had diabetes, 1,326 (14%) had isolated systolic hypertension, 1,469 (16%) had coronary heart disease, and 728 (8%) had cerebrovascular disease. Baseline mean blood pressure was 174/98 mmHg in both treatment groups. The mean length of follow-up was 4.8 years. At the end of study or at the last visit before a primary endpoint, 77% of the group treated with losartan and 73% of the group treated with atenolol were still taking study medication. Of the patients still taking study medication, the mean doses of losartan and atenolol were both about 80 mg/day, and 15% were taking atenolol or losartan as monotherapy, while 77% were also receiving hydrochlorothiazide (at a mean dose of 20 mg/day in each group). Blood pressure reduction measured at trough was similar for both treatment groups but blood pressure was not measured at any other time of the day. At the end of study or at the last visit before a primary endpoint, the mean blood pressures were 144.1/81.3 mmHg for the group treated with losartan and 145.4/80.9 mmHg for the group treated with atenolol; the difference in systolic blood pressure (SBP) of 1.3 mmHg was significant (p<0.001), while the difference of 0.4 mmHg in diastolic blood pressure (DBP) was not significant (p=0.098).

The primary endpoint was the first occurrence of cardiovascular death, nonfatal stroke, or nonfatal myocardial infarction. Patients with nonfatal events remained in the trial, so that there was also an examination of the first event of each type even if it was not the first event (e.g., a stroke following an initial myocardial infarction would be counted in the analysis of stroke). Treatment with losartan resulted in a 13% reduction (p=0.021) in risk of the primary endpoint compared to the atenolol group (see Figure 1 and Table 3); this difference was primarily the result of an effect on fatal and nonfatal stroke. Treatment with losartan reduced the risk of stroke by 25% relative to atenolol (p=0.001) (see Figure 2 and Table 3).

Figure 1: Kaplan-Meier estimates of the primary endpoint of time to cardiovascular death, nonfatal stroke, or nonfatal myocardial infarction in the groups treated with losartan and atenolol. The Risk Reduction is adjusted for baseline Framingham risk score and level of electrocardiographic left ventricular hypertrophy.

Figure 2: Kaplan-Meier estimates of the time to fatal/nonfatal stroke in the groups treated with losartan and atenolol. The Risk Reduction is adjusted for baseline Framingham risk score and level of electrocardiographic left ventricular hypertrophy.

Table 3 shows the results for the primary composite endpoint and the individual endpoints. The primary endpoint was the first occurrence of stroke, myocardial infarction or cardiovascular death, analyzed using an ITT approach. The table shows the number of events for each component in two different ways. The Components of Primary Endpoint (as a first event) counts only the events that define the primary endpoint, while the Secondary Endpoints count all first events of a particular type, whether or not they were preceded by a different type of event.

Table 3: Incidence of Primary Endpoint Events

 | Losartan |  | Atenolol |  | Risk Reduction† | 95%; CI | p-Value
 | N (%) | Rate* | N (%) | Rate*
Primary Composite Endpoint | 508 (11) | 23.8 | 588 (13) | 27.9 | 13% | 2% to 23% | 0.021
Components of Primary Composite Endpoint (as a first event)
Stroke (nonfatal) | 209 (5) |  | 286 (6)
Myocardial infarction (nonfatal) | 174 (4) |  | 168 (4)
Cardiovascular mortality | 125 (3) |  | 134 (3)
Secondary Endpoints (any time in study)
Stroke (fatal/nonfatal) | 232 (5) | 10.8 | 309 (7) | 14.5 | 25% | 11% to 37% | 0.001
Myocardial infarction (fatal/nonfatal) | 198 (4) | 9.2 | 188 (4) | 8.7 | -7% | -13% to 12% | 0.491
Cardiovascular mortality | 204 (4) | 9.2 | 234 (5) | 10.6 | 11% | -7% to 27% | 0.206
Due to CHD | 125 (3) | 5.6 | 124 (3) | 5.6 | -3% | -32% to 20% | 0.839
Due to Stroke | 40 (1) | 1.8 | 62 (1) | 2.8 | 35% | 4% to 67% | 0.032
Other‡ | 39 (1) | 1.8 | 48 (1) | 2.2 | 16% | -28% to 45% | 0.411

* Rate per 1,000 patient-years of follow-up

† Adjusted for baseline Framingham risk score and level of electrocardiographic left ventricular hypertrophy

‡ Death due to heart failure, non-coronary vascular disease, pulmonary embolism, or a cardiovascular cause other than stroke or coronary heart disease

Although the LIFE study favored losartan over atenolol with respect to the primary endpoint (p=0.021), this result is from a single study and, therefore, is less compelling than the difference between losartan and placebo. Although not measured directly, the difference between losartan and placebo is compelling because there is evidence that atenolol is itself effective (vs. placebo) in reducing cardiovascular events, including stroke, in hypertensive patients.

Other clinical endpoints of the LIFE study were: total mortality, hospitalization for heart failure or angina pectoris, coronary or peripheral revascularization procedures, and resuscitated cardiac arrest. There were no significant differences in the rates of these endpoints between the losartan and atenolol groups.

For the primary endpoint and stroke, the effects of losartan in patient subgroups defined by age, gender, race and presence or absence of isolated systolic hypertension (ISH), diabetes, and history of cardiovascular disease (CVD) are shown in Figure 3 below. Subgroup analyses can be difficult to interpret and it is not known whether these represent true differences or chance effects.

Figure 3: Primary Endpoint Events† within Demographic Subgroups

Symbols are proportional to sample size.

#Other includes Asian, Hispanic, Asiatic, Multi-race, Indian, Native American, European.

†Adjusted for baseline Framingham risk score and level of electrocardiographic left ventricular hypertrophy.

14.3 Nephropathy in Type 2 Diabetic Patients

The RENAAL study was a randomized, placebo-controlled, double-blind, multicenter study conducted worldwide in 1,513 patients with type 2 diabetes with nephropathy (defined as serum creatinine 1.3 to

3 mg/dL in females or males ≤60 kg and 1.5 to 3 mg/dL in males >60 kg and proteinuria [urinary albumin to creatinine ratio ≥300 mg/g]).

Patients were randomized to receive losartan50 mg once daily or placebo on a background of conventional antihypertensive therapy excluding ACE inhibitors and angiotensin II antagonists. After one month, investigators were instructed to titrate study drug to 100 mg once daily if the trough blood pressure goal (140/90 mmHg) was not achieved. Overall, 72% of patients received the 100-mg daily dose more than 50% of the time they were on study drug. Because the study was designed to achieve equal blood pressure control in both groups, other antihypertensive agents (diuretics, calcium-channel blockers, alpha-or beta-blockers, and centrally acting agents) could be added as needed in both groups. Patients were followed for a mean duration of 3.4 years.

The study population was diverse with regard to race (Asian 16.7%, Black 15.2%, Hispanic 18.3%, White 48.6%). Overall, 63.2% of the patients were men, and 66.4% were under the age of 65 years. Almost all of the patients (96.6%) had a history of hypertension, and the patients entered the trial with a mean serum creatinine of 1.9 mg/dL and mean proteinuria (urinary albumin/creatinine) of 1,808 mg/g at baseline.

The primary endpoint of the study was the time to first occurrence of any one of the following events: doubling of serum creatinine, end-stage renal disease (ESRD) (need for dialysis or transplantation), or death. Treatment with losartan resulted in a 16% risk reduction in this endpoint (see Figure 4 and Table 4). Treatment with losartan also reduced the occurrence of sustained doubling of serum creatinine by 25% and ESRD by 29% as separate endpoints, but had no effect on overall mortality (see Table 4).

The mean baseline blood pressures were 152/82 mmHg for losartan plus conventional antihypertensive therapy and 153/82 mmHg for placebo plus conventional antihypertensive therapy. At the end of the study, the mean blood pressures were 143/76 mmHg for the group treated with losartan and 146/77 mmHg for the group treated with placebo.

Figure 4: Kaplan-Meier curve for the primary composite endpoint of doubling of serum creatinine, end stage renal disease (need for dialysis or transplantation) or death.

Table 4: Incidence of Primary Endpoint Events

 | Incidence |  | Risk Reduction | 95% C.I. | p-Value
 | Losartan | Placebo
Primary Composite Endpoint | 43.5% | 47.1% | 16.1% | 2.3% to 27.9% | 0.022
Doubling of Serum Creatinine, ESRD and Death Occurring as a First Event
Doubling of Serum Creatinine | 21.6% | 26.0%
ESRD | 8.5% | 8.5%
Death | 13.4% | 12.6%
Overall Incidence of Doubling of Serum Creatinine, ESRD and Death
Doubling of Serum Creatinine | 21.6% | 26.0% | 25.3% | 7.8% to 39.4% | 0.006
ESRD | 19.6% | 25.5% | 28.6% | 11.5% to 42.4% | 0.002
Death | 21.0% | 20.3% | -1.7% | -26.9% to 18.6% | 0.884

The secondary endpoints of the study were change in proteinuria, change in the rate of progression of renal disease, and the composite of morbidity and mortality from cardiovascular causes (hospitalization for heart failure, myocardial infarction, revascularization, stroke, hospitalization for unstable angina, or cardiovascular death). Compared with placebo, losartan significantly reduced proteinuria by an average of 34%, an effect that was evident within 3 months of starting therapy, and significantly reduced the rate of decline in glomerular filtration rate during the study by 13%, as measured by the reciprocal of the serum creatinine concentration. There was no significant difference in the incidence of the composite endpoint of cardiovascular morbidity and mortality.

The favorable effects of losartan were seen in patients also taking other anti-hypertensive medications (angiotensin II receptor antagonists and angiotensin converting enzyme inhibitors were not allowed), oral hypoglycemic agents and lipid-lowering agents.

For the primary endpoint and ESRD, the effects of losartan in patient subgroups defined by age, gender and race are shown in Table 5 below. Subgroup analyses can be difficult to interpret and it is not known whether these represent true differences or chance effects.

Table 5: Efficacy Outcomes within Demographic Subgroups

 | No. of Patients | Primary Composite Endpoint |  |  | ESRD
 |  | Losartan Event Rate % | Placebo Event Rate % | Hazard Ratio (95% CI) | Losartan Event Rate % | Placebo Event Rate % | Hazard Ratio (95% CI)
Overall Results | 1,513 | 43.5 | 47.1 | 0.84 (0.72, 0.98) | 19.6 | 25.5 | 0.71 (0.58, 0.89)
Age
<65 years | 1,005 | 44.1 | 49.0 | 0.78 (0.65, 0.94) | 21.1 | 28.5 | 0.67 (0.52, 0.86)
≥65 years | 508 | 42.3 | 43.5 | 0.98 (0.75, 1.28) | 16.5 | 19.6 | 0.85 (0.56, 1.28)
Gender
Female | 557 | 47.8 | 54.1 | 0.76 (0.60, 0.96) | 22.8 | 32.8 | 0.60 (0.44, 0.83)
Male | 956 | 40.9 | 43.3 | 0.89 (0.73, 1.09) | 17.5 | 21.5 | 0.81 (0.60, 1.08)
Race
Asian | 252 | 41.9 | 54.8 | 0.66 (0.45, 0.95) | 18.8 | 27.4 | 0.63 (0.37, 1.07)
Black | 230 | 40.0 | 39.0 | 0.98 (0.65, 1.50) | 17.6 | 21.0 | 0.83 (0.46, 1.52)
Hispanic | 277 | 55.0 | 54.0 | 1.00 (0.73, 1.38) | 30.0 | 28.5 | 1.02 (0.66, 1.59)
White | 735 | 40.5 | 43.2 | 0.81 (0.65, 1.01) | 16.2 | 23.9 | 0.60 (0.43, 0.83)

16 HOW SUPPLIED

Arbli (losartan potassium)is a white, translucent oral suspension. Each mL contains 10 mg losartan potassium (equivalent to 9.2 mg losartan). It is supplied as 165 mL in a high-density polyethylene (HDPE) bottle with a child-resistant cap and tamper-evident seal. Shake for 20 seconds prior to each use.

NDC 83245-053-06

Store at 20°C to 25°C (68°F to 77°F); excursions permitted between 15°C to 30°C (59°F to 86°F) [see USP Controlled Room Temperature]. Keep container tightly closed. Protect from light.

Store and dispense in original container. Once the bottle is opened, use it within 60 days.

17 PATIENT COUNSELING INFORMATION

Administration Information

Instruct patients or caregivers to use oral dosing syringe(s) or an oral dosing cup to correctly measure the prescribed amount of medication. Inform patients that oral dosing syringe(s) or an oral dosing cup may be obtained from their pharmacy.

Pregnancy

Advise pregnant women and females of reproductive potential of the potential risk to the fetus and to inform their healthcare providers of a known, suspected, or planned pregnancy during treatment with losartan [see Warning and Precautions (5.3) and Use in Specific Population (8.1)].

Lactation

Advise women not to breastfeed during treatment with Arbli and for 2 days after the last dose [see Use in Specific Populations (8.2)].

Potassium Supplements

Advise patients receiving losartan not to use potassium supplements or salt substitutes containing potassium without consulting their healthcare provider [see Drug Interactions (7.1)].

Manufactured for:

Scienture LLC

Commack, NY 11725

Distributed by:

Scienture LLC

Commack, NY 11725

10/25-R1

PPM-0085